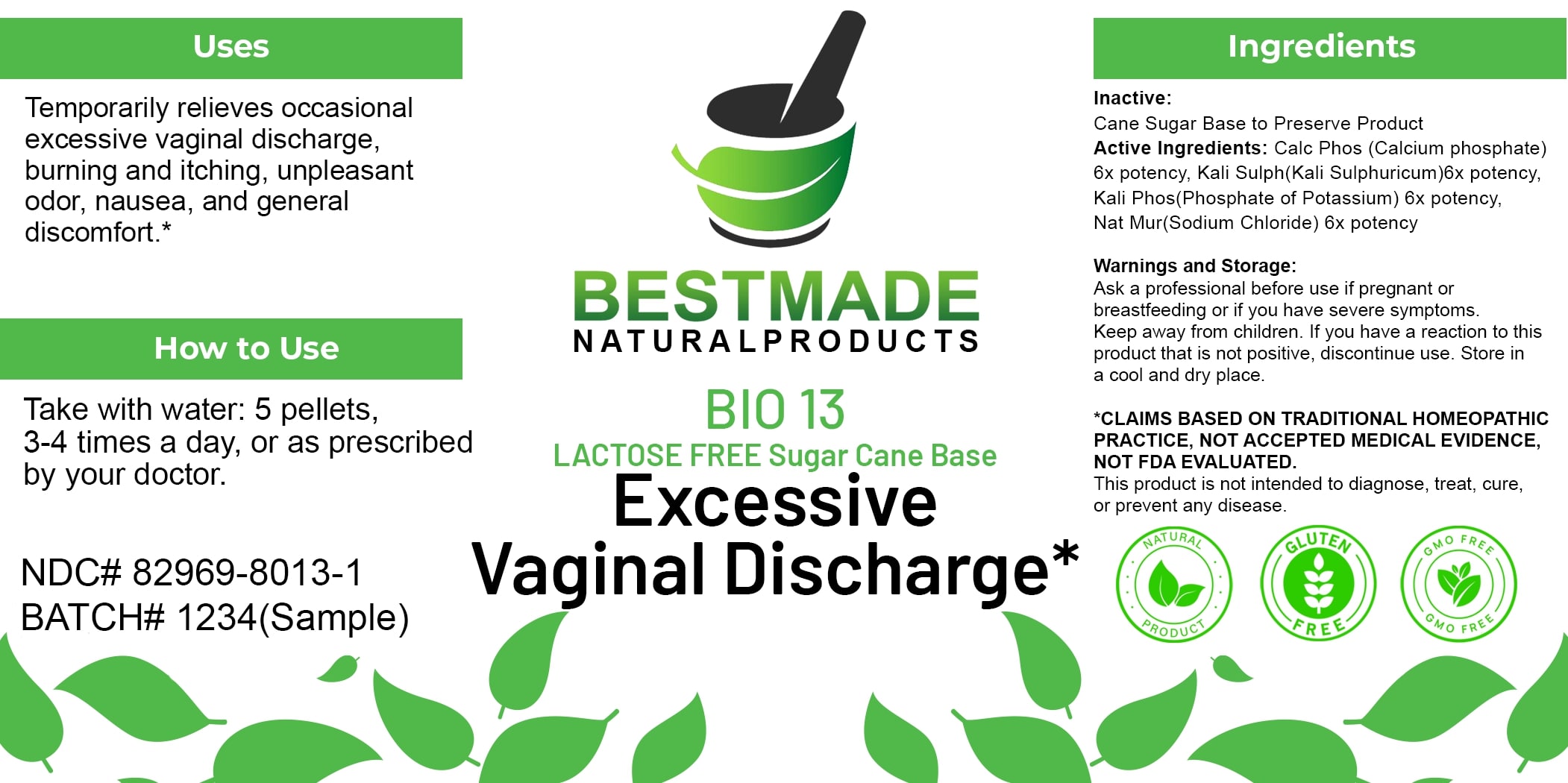 DRUG LABEL: Bestmade Natural Products BIO13 Lactose Free
NDC: 82969-8013 | Form: TABLET, SOLUBLE
Manufacturer: Bestmade Natural Products
Category: homeopathic | Type: HUMAN OTC DRUG LABEL
Date: 20250323

ACTIVE INGREDIENTS: TRIBASIC CALCIUM PHOSPHATE 6 [hp_X]/6 [hp_X]; POTASSIUM SULFATE 6 [hp_X]/6 [hp_X]; SODIUM CHLORIDE 6 [hp_X]/6 [hp_X]; DIBASIC POTASSIUM PHOSPHATE 6 [hp_X]/6 [hp_X]
INACTIVE INGREDIENTS: SUCROSE 6 [hp_X]/6 [hp_X]

BIO13 Excessive Vaginal Discharge* LACTOSE FREE Sugar Cane Base

DOSAGE AND ADMINISTRATION

How to Use

Take with water: 5 pellets, 3-4 times a day, or as prescribed by your doctor.

Inactive:

Cane Sugar Base to Preserve Product

Active Ingredients:

Calc Phos (Calcium phosphate) 6x potency, Kali Sulph (Kali Sulphuricum6x potency, Kali Phos (Phosphate of Potassium) 6x potency, Nat Mur (Sodium Chloride) 6x potency

Uses

Temporarily relieves occasional excessive vaginal discharge burning and itching, unpleasant odor, nausea, and general discomfort.*

*CLAIMS BASED ON TRADITIONAL HOMEOPATHIC PRACTICE, NOT ACCEPTED MEDICAL EVIDENCE, NOT FDA EVALUATED.

This product is not intended to diagnose, treat, cure, or prevent any disease.

Uses

Temporarily relieves occasional excessive vaginal discharge burning and itching, unpleasant odor, nausea, and general discomfort.*

*CLAIMS BASED ON TRADITIONAL HOMEOPATHIC PRACTICE, NOT ACCEPTED MEDICAL EVIDENCE, NOT FDA EVALUATED.

This product is not intended to diagnose, treat, cure, or prevent any disease.

KEEP OUT OF REACH OF CHILDREN

Warnings and Storage:

Ask a professional before use if pregnant or breastfeeding or if you have severe symptoms. Keep away from children. If you have a reaction to this product that is not positive, discontinue use. Store in a cool and dry place.

Warnings and Storage:

Ask a professional before use if pregnant or breastfeeding or if you have severe symptoms. Keep away from children. If you have a reaction to this product that is not positive, discontinue use. Store in a cool and dry place.

*CLAIMS BASED ON TRADITIONAL HOMEOPATHIC PRACTICE, NOT ACCEPTED MEDICAL EVIDENCE NOT FDA EVALUATED.

This product is not intended to diagnose, treat, cure, or prevent any disease.

Entire package label